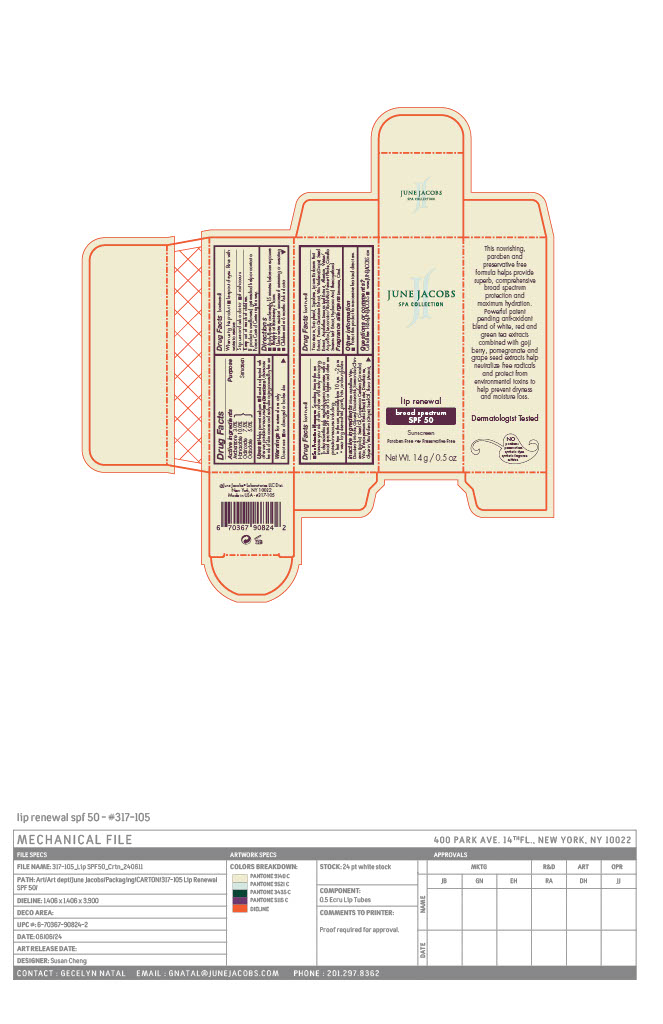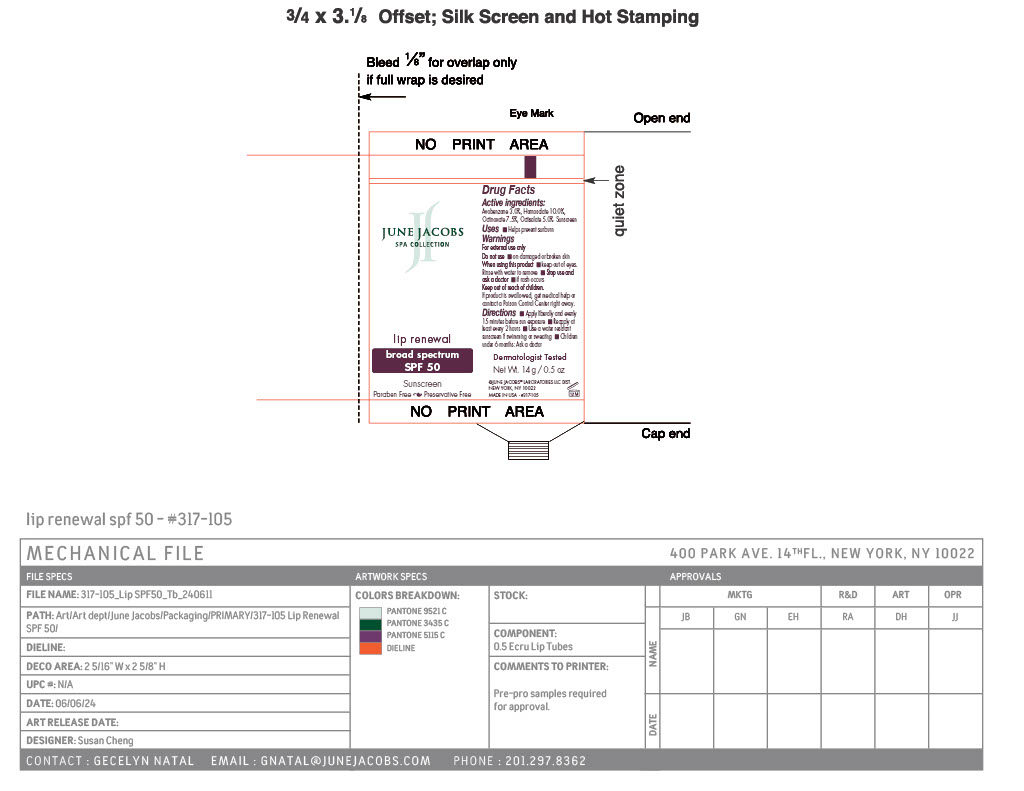 DRUG LABEL: Lip Renewal SPF 50
NDC: 65278-105 | Form: PASTE
Manufacturer: June Jacobs Labs, LLC
Category: otc | Type: HUMAN OTC DRUG LABEL
Date: 20240515

ACTIVE INGREDIENTS: OCTINOXATE 1.05 g/14 g; AVOBENZONE 0.42 g/14 g; HOMOSALATE 1.4 g/14 g; OCTISALATE 0.7 g/14 g
INACTIVE INGREDIENTS: PHENOXYETHANOL; HYALURONIC ACID; WATER; LIMONENE, (+)-; MENTHOL; VANILLIN; LYCIUM BARBARUM FRUIT; GLYCERYL DIISOSTEARATE; DIMETHICONE; GRAPE SEED OIL; DIISOSTEARYL MALATE; SPEARMINT OIL; CARVONE, (+/-)-; TRIISOSTEARIN; TOCOPHEROL; ASPALATHUS LINEARIS LEAF; LEUCONOSTOC/RADISH ROOT FERMENT FILTRATE; GLYCERIN; CITRAL; MICROCRYSTALLINE WAX; SHEA BUTTER; PUNICA GRANATUM ROOT BARK; ALLANTOIN; GREEN TEA LEAF; JOJOBA OIL; CARNAUBA WAX; SQUALANE; VITIS VINIFERA SEED

Lip Renewal SPF 50

Active Ingredients

Avobenzone...........................3.0%

Homosalate...........................10.0%

Octinoxate.............................7.5%

Octisalate..............................5.0%

PURPOSE

Sunscreen

Uses

- Helps prevent sunburn
- If used as directed with other sun protection measures (See Directions), decreases the risk of skin cancer and early skin aging caused by the sun

Warnings

For External use only

Do not use on

- damaged or broken skin

When using this product

- Keep out of eyes. Rinse with water to remove.

Keep out of reach of children.

If product is swallowed, get madical help or contact a poison control center right away.

Directions

- Apply liberally and evenly every 15 minutes before sun exposure
- Reapply at least every 2 hours
- Use a water resistant sunscreen if swimming or sweating
- Children under 6 months: Ask a doctor
- Sun Protection measures. Spending time in the sun increases your risk of skin cancer and early skin aging. To decrease this risk, regularly use as sunscreen with a broad spectrum SPF value of 15 or higher and other sun protection measures including:
- limit time in the sun especially from 10am -2 pm.
- wear long sleeve shirt, pants hats and sunglasses

Inactive Ingredients

Microcrystalline Wax, Diisostearyl Malate, Glyceryl Diisostearate, Simmondsia Chinensis (Jojoba) Seed Oil, Copernicia Cerifera (Carnauba) Wax, Butyrospermum Parkii (Shea) Butter, Dimethicone, Glycerin, Vitis Vinifera (Grape) Seed Oil, Flavor (Aroma), Triisostearin, Tocopherol, Squalane, Lycium Barbarum Fruit Extract, Punica Granatum Extract, Vitis Vinifera (Grape) Seed Extract, Aspalathus Linearis Leaf Extract, Allantoin, Water/ Aqua, Leuconostoc/Radish Root Ferment Filtrate, Camellia Sinensis Leaf Extract, Hyaluronic Acid, Phenoxyethanol, Limonene, Citral

Other Information

- Protect this product from excessive heat and direct sun.

Questions or comments?

Call toll free 1-866-JUNEJACOBS

- www.JUNEJACOBS.com